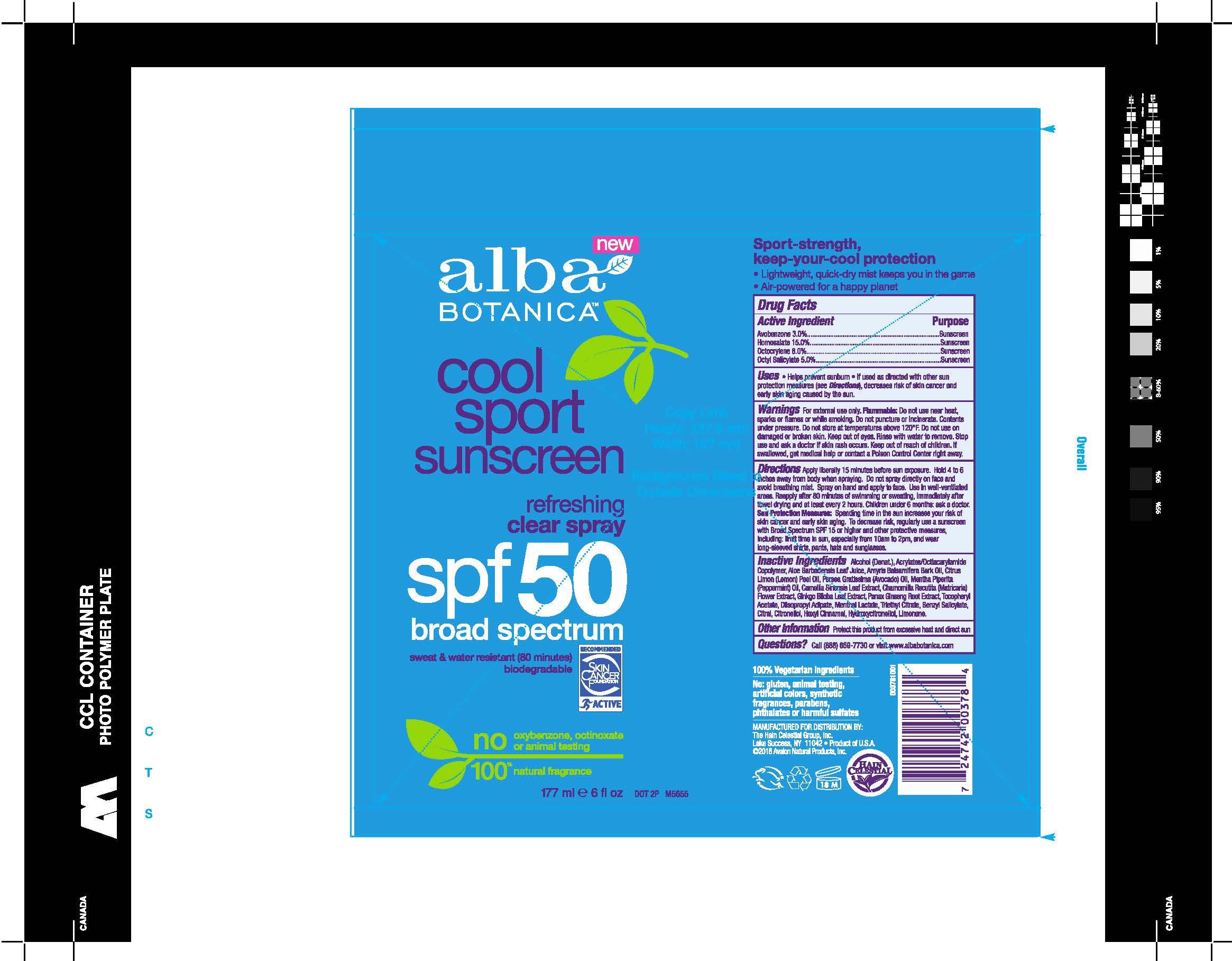 DRUG LABEL: AL00378 Alba Cool Sport Sunscreen SPF50
NDC: 61995-2378 | Form: SPRAY
Manufacturer: The Hain Celestial Group, Inc.
Category: otc | Type: HUMAN OTC DRUG LABEL
Date: 20210205

ACTIVE INGREDIENTS: OCTOCRYLENE 8 g/100 g; OCTISALATE 5 g/100 g; AVOBENZONE 3 g/100 g; HOMOSALATE 15 g/100 g
INACTIVE INGREDIENTS: CHAMOMILE; TRIETHYL CITRATE; ALOE VERA LEAF; GREEN TEA LEAF; GINKGO; ASIAN GINSENG; .ALPHA.-TOCOPHEROL ACETATE; ALCOHOL; DIISOPROPYL ADIPATE; LIMONENE, (+)-; AMYRIS BALSAMIFERA OIL; LEMON OIL; AVOCADO OIL; PEPPERMINT OIL; MENTHYL LACTATE, (-)-

Alba Cool Sport SPF 50 Sunscreen

ACTIVE INGREDIENT

Avobenzone 3.0%

Homosalate 15.0%

Octocrylene 8.0%

Octyl Salicylate 5.0%

PURPOSE

Sunscreen

INDICATIONS AND USAGE

- Helps prevent sunburn. If uses as directed with other sun protection measures (see Directions), decreases risk of skin cancer and early skin aging caused by the sun.

WARNINGS

For external use only. Flammable.Do not use near heat, sparks or flames or while smoking. Do not puncture orincinerate. Contents under preassure .Do not store at temperature above 120°C. Do not use on damaged or broken skin. When using this product keep out of eye. Rinse with water to remove. Stop use and ask a doctor if skin rash occurs.

Keep out of reach of children. If swallowed, get medical help or contact a Poison Control Center right away

DOSAGE AND ADMINISTRATION

Apply liberally 15 minutes before sun exposure.Hold 4 to 6 inches away from body when spraying. Do not spray directly on face and avoid breathing mist. Spray on hand and apply to face. Use in well- ventilated areas. Reapply after 80 min of swimming or sweating, immediately after towel drying and at lease every two hrs. Children under 6 months: ask a doctor.

Skin protection measures:

Spending time in the sun increases your risk of skin cancer and early skin aging. To decrease a risk,regularly use a Sunscreen with Broad Spectrum SPF 15 or higher and other protective measures including: limit time in sun, especially 10am- 2pm, wear long- sleeved shirts,pants, hats and sunglasses.

INACTIVE INGREDIENT

Alcohol, Acrylates/Octylacrylamide Copolymer, Persea Gratissima (Avocado) Oil, Diisopropyl Adipate, Citrus Limon (lemon) Oil, Aloe Barbadensis Leaf Juice, Amyris Balsamifera Bark Oil, Camellia Sinensis Leaf Extract, Chamomilla Recuitita (Matricaria) Flower Extract, Panax Ginseng Root Extract, Gingko Biloba Root Extract, Tocopheryl Acetate, Triethyl Citrate, Benzyl Salicylate, Citral, Citronellol, Hexyl Cinnamal, Hydroxycitronellol, Limonene.

QUESTIONS

Questions? Call 888-659-7730 or visit www.albabotanica.com